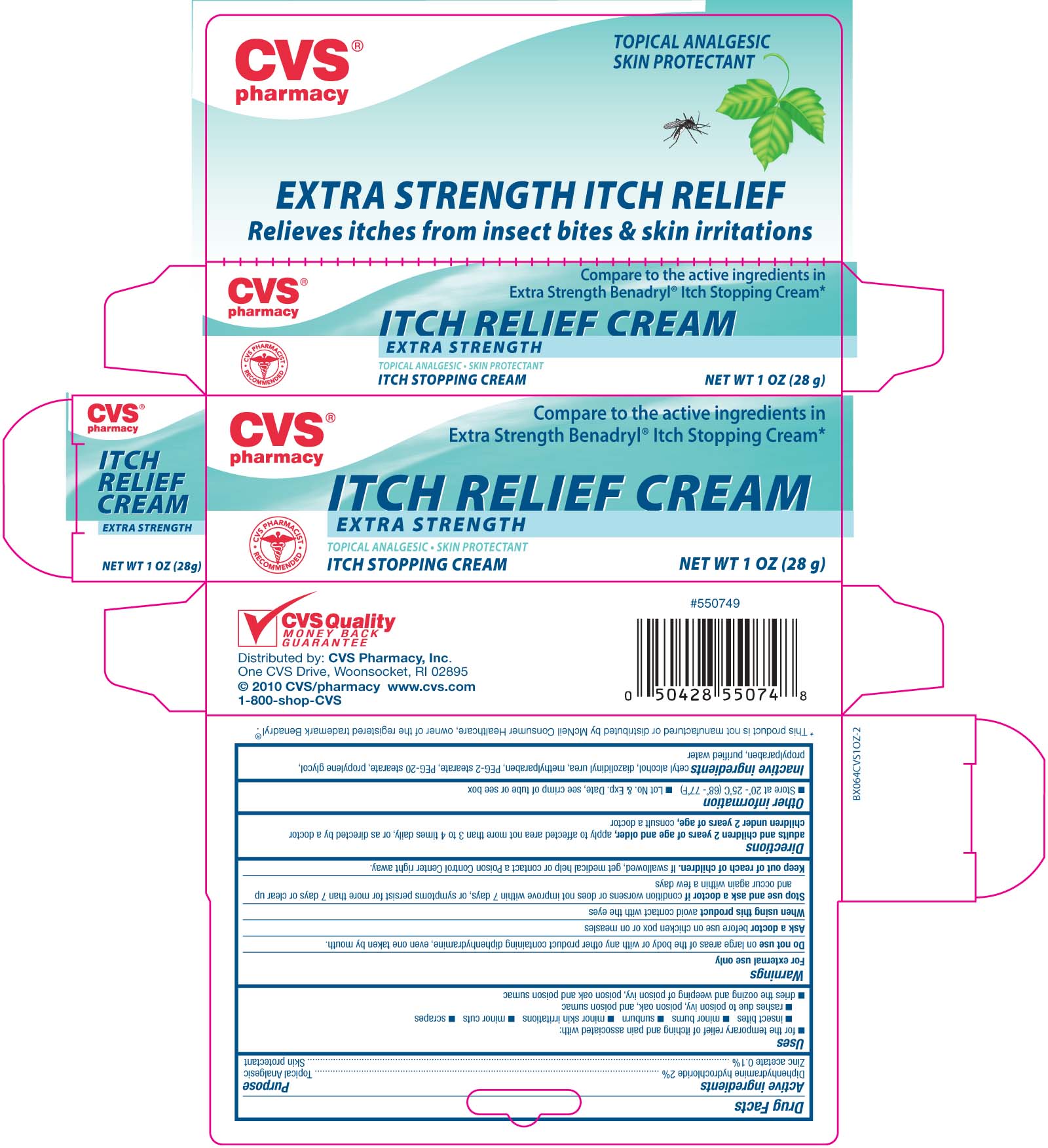 DRUG LABEL: CVS Extra Strength Itch Relief
NDC: 59779-053 | Form: OINTMENT
Manufacturer: CVS Pharmacy
Category: otc | Type: HUMAN OTC DRUG LABEL
Date: 20100913

ACTIVE INGREDIENTS: DIPHENHYDRAMINE HYDROCHLORIDE 20 mg/1 g; ZINC ACETATE 12 mg/1 g
INACTIVE INGREDIENTS: WATER; CETYL ALCOHOL; STEARETH-2; PROPYLENE GLYCOL; STEARETH-100; DIAZOLIDINYL UREA

DRUG FACTS

Active ingredient Purpose
Diphenhydramine hydrochloride 2%...................Topical Analgesic
Zinc acetate....................................................Skin protectant

Uses
- for the temporary relief of itching and pain associated with:
-insect bites - minor burns - sunburn - minor skin irritations - minor cuts - scrapes
- rashes due to poison ivy, poison oak, and poison sumac
- dries the oozing and weeping of poison ivy, poison oak and poison sumac

Keep out of reach of children. If swallowed, get medical help or contact a
Poison Control Center right away.

Uses
- for the temporary relief of itching and pain associated with:
-insect bites - minor burns - sunburn - minor skin irritations - minor cuts - scrapes
- rashes due to poison ivy, poison oak, and poison sumac
- dries the oozing and weeping of poison ivy, poison oak and poison sumac

Warnings
For external use only
Do not use on large areas of the body or with any other product containing diphenhydramine,
even one taken by mouth
Ask a doctor before use on chicken pox or on measles
When using this product avoid contact with the eyes
Stop use and ask a doctor if condition worsens or does not improve within 7 days,
or symptoms persist for ore than 7 days or clear up and occur again within a few days.
Keep out of reach of children.If swallowed, get medical help or contact a
Poison Control Center right away.

Directions
adults and children 2 years and older, apply to affected area not more than 3 to 4 times daily, or as directed by a doctor
children under 2 years of age: consult a doctor
Other information
- store at 20 degrees - 25 degrees C (68 to 70 degrees F) - Lot No. and Exp. Date, see crimp of tube or see box

Inactive Ingredients
cetyl alcohol, diazolidinyl urea, methylparaben, PEG-2 stearate, PEG-20 stearate,
propylene glycol, propylparaben, purified water